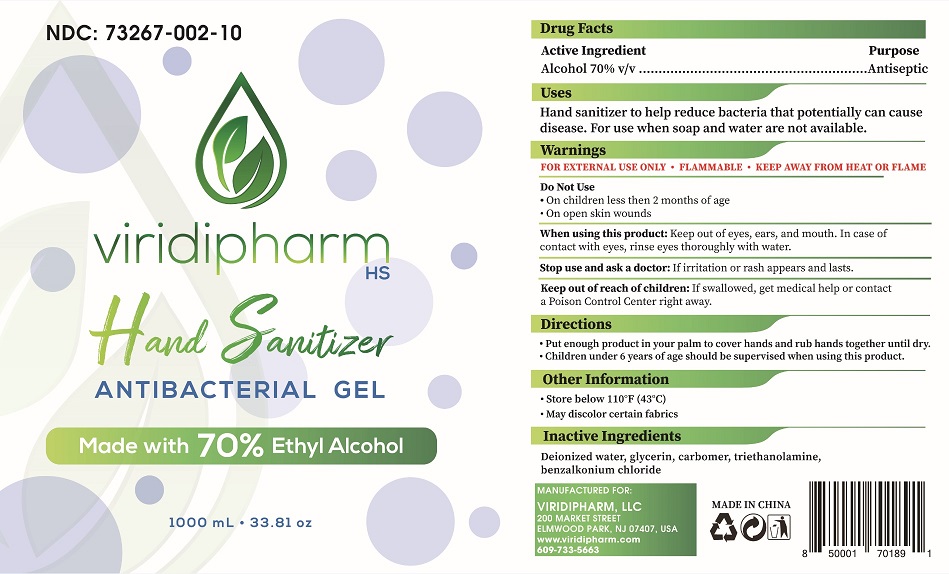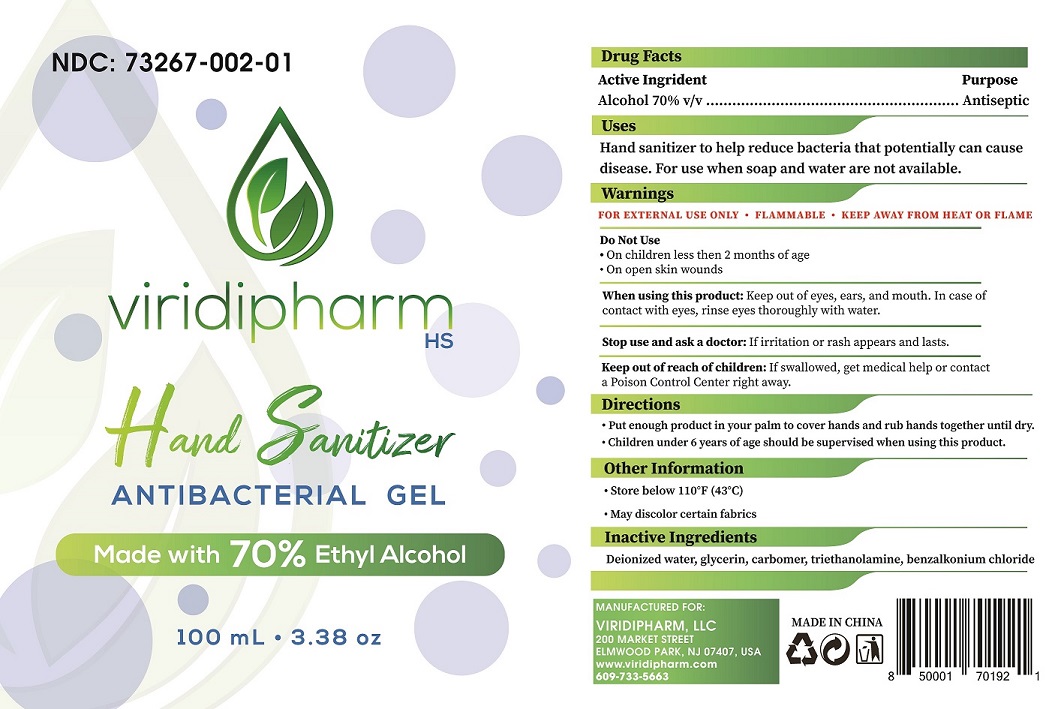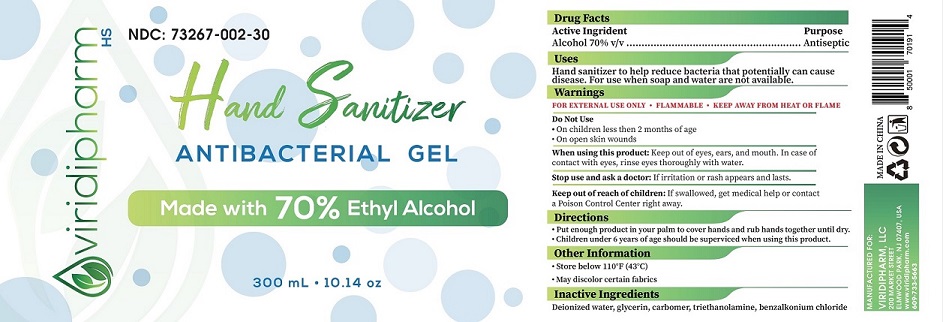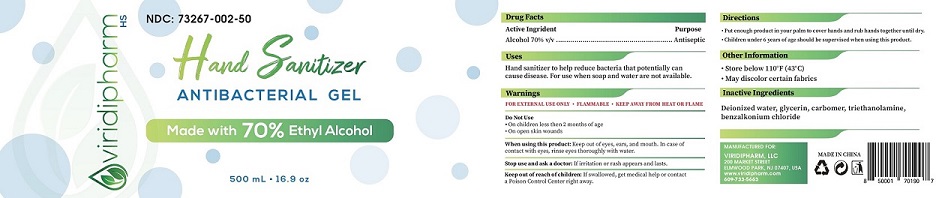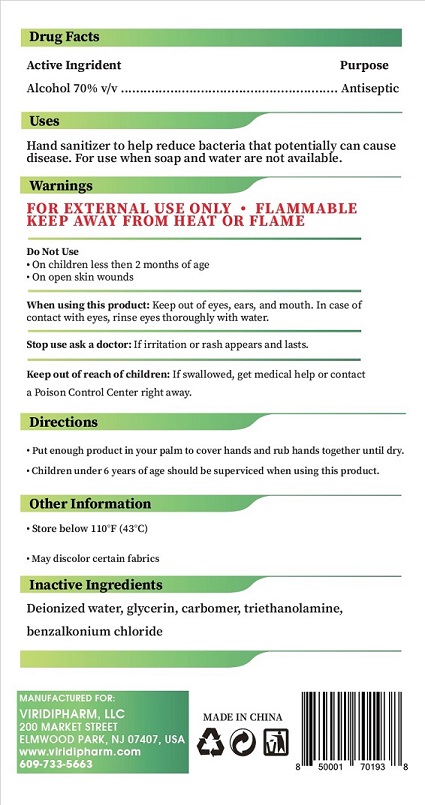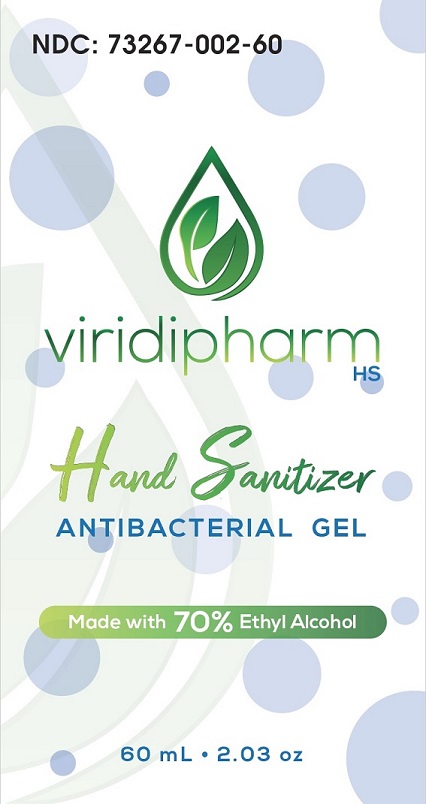 DRUG LABEL: Viridipharm Hand Sanitizer Antibacterial Gel
NDC: 73267-002 | Form: GEL
Manufacturer: VIRIDIPHARM, LLC
Category: otc | Type: HUMAN OTC DRUG LABEL
Date: 20201110

ACTIVE INGREDIENTS: ALCOHOL 70 mL/100 mL
INACTIVE INGREDIENTS: CARBOMER HOMOPOLYMER, UNSPECIFIED TYPE; GLYCERIN; WATER; TROLAMINE; BENZALKONIUM CHLORIDE

Active Ingredient(s)

Alcohol 70% v/v

Purpose

Antiseptic

Use(s)

- Hand sanitizer to help reduce bacteria on the skin that potentially can cause disease. For use when soap water are not available.

Warnings

For external use only. Flammable. Keep away from heat or flame.

Do Not Use

*On children less then 2 months of age

*On open skin wounds

When using this product: Keep out of eyes, ears,a nd mouth. In case of contact with eyes, rinse eyes thoroughly with water.

Stop use and ask a doctor: If irritation or rash appears and lasts.

Keep out of reach of children: If swallowed, get medical help or contact a Poison Control Center right away.

Directions

*Put enough product in your palm to cover hands and rub hands together until dry.

*Children under 6 years of age should be supervised when using this product.

Other information

*Store below 110°F (43°C)

*May discolor certain fabric

Inactive ingredients

Deionized water, glycerin carbomer, triethanolamine, benzalkonium chloride